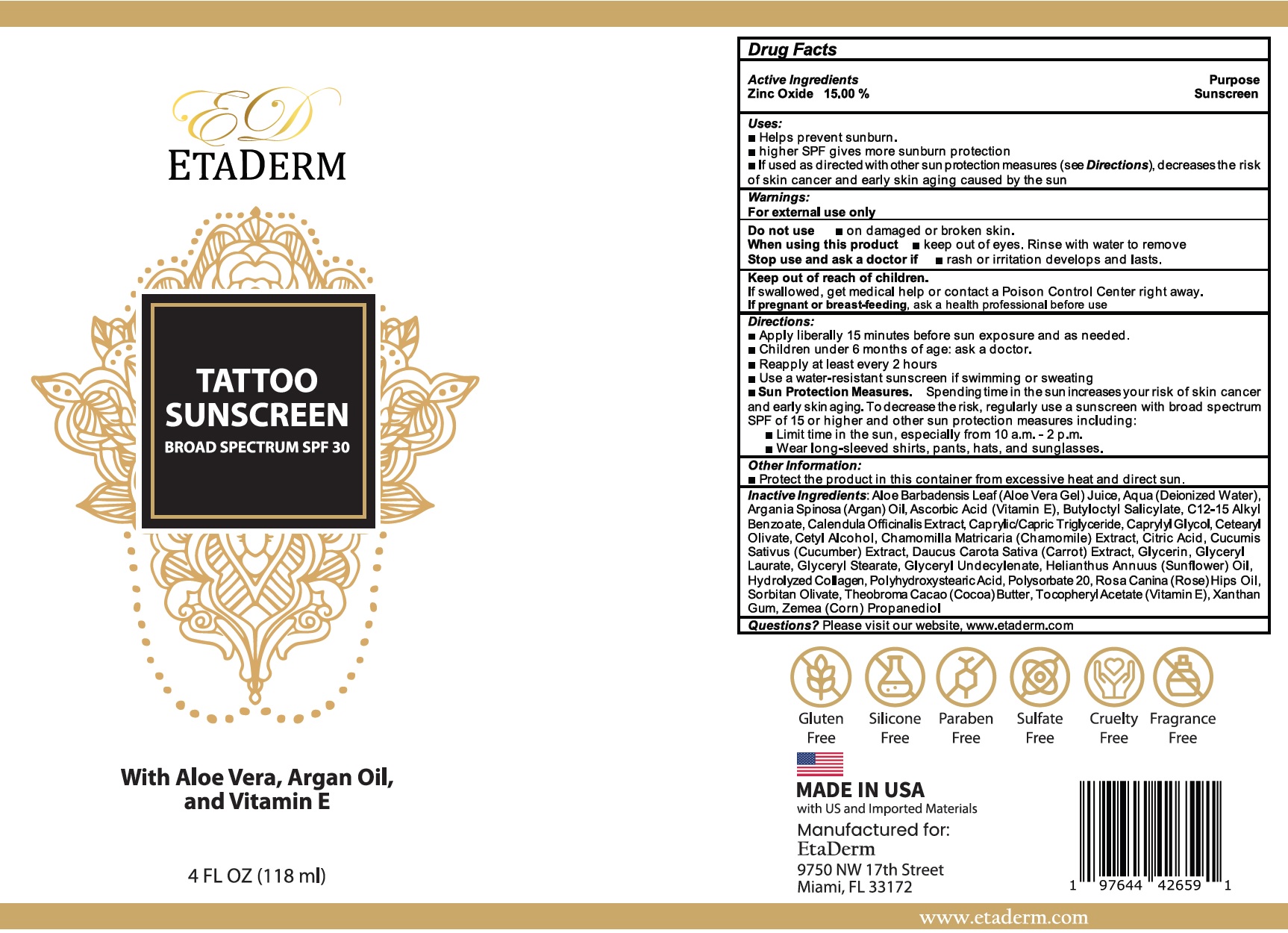 DRUG LABEL: ETADERM Tattoo Sunscreen Broad Spectrum SPF-30
NDC: 84180-472 | Form: CREAM
Manufacturer: NUEPHASE LLC
Category: otc | Type: HUMAN OTC DRUG LABEL
Date: 20240320

ACTIVE INGREDIENTS: ZINC OXIDE 150 mg/1 mL
INACTIVE INGREDIENTS: ALOE VERA LEAF; WATER; ASCORBIC ACID; BUTYLOCTYL SALICYLATE; ALKYL (C12-15) BENZOATE; CALENDULA OFFICINALIS FLOWER; MEDIUM-CHAIN TRIGLYCERIDES; CAPRYLYL GLYCOL; CETEARYL OLIVATE; CETYL ALCOHOL; CHAMOMILE; CITRIC ACID MONOHYDRATE; CUCUMBER; CARROT; GLYCERIN; GLYCERYL LAURATE; GLYCERYL MONOSTEARATE; HELIANTHUS ANNUUS FLOWERING TOP; POLYSORBATE 20; SORBITAN OLIVATE; COCOA; .ALPHA.-TOCOPHEROL ACETATE; XANTHAN GUM; CORN

ETADERM Tattoo Sunscreen Broad Spectrum SPF-30

Active Ingredients

Zinc Oxide 15.00%

Purpose

Sunscreen

Uses:

- Helps prevent sun burn.
- higher SPF gives more sun burn protection
- If used as directed with other sun protection measures (see Directions), decreases the risk of skin cancer and early skin aging caused by the sun

Warnings:

For external use only

Do not use

- on damaged or broken skin.

When using this product

- keep out of eyes. Rinse with water to remove

Stop use and ask a doctor if

- rash or irritation develops and lasts.

Keep out of reach of children.

If swallowed, get medical help or contact a Poison Control Center right away.

If pregnant or breast-feeding,

ask a health professional before use

Directions:

- Apply liberally15 minutes before sun exposure and as needed.
- Children under 6 months of age: ask a doctor.
- Reapply: at least every 2 hours.
- Use a water-resistant sunscreen if swimming or sweating
- Sun Protection Measures.Spending time in the sun increases your risk of skin cancer and early skin aging. To decrease this risk, regularly use a sunscreen with broad spectrum SPF of 15 or higher and other sun protection measures including:
- Limit time in the sun, especially from 10 a.m.-2 p.m.
- Wear long-sleeved shirts, pants, hats, and sunglasses.

Other Information:

- Protect the product in this container from excessive heat and direct sun.

Inactive Ingredients:

Aloe Barbadensis Leaf (Aloe Vera Gel) Juice, Aqua (Deionized Water), Argania Spinosa (Argan) Oil, Ascorbic Acid (Vitamin E), Butyloctyl Salicylate, C12-15 Alkyl Benzoate, Calendula Officinalis Extract, Caprylic/Capric Triglyceride, Caprylyl Glycol, Cetearyl Olivate, Cetyl Alcohol, Chamomilla Matricaria (Chamomile) Extract, Citric Acid, Cucumis Sativus (Cucumber) Extract, Daucus Carota Sativa (Carrot) Extract, Glycerin, Glyceryl Laurate, Glyceryl Stearate, Glyceryl Undecylenate, Helianthus Annuus (Sun flower) Oil, Hydrolyzed Collagen, Polyhydroxy stearic Acid, Polysorbate 20, Rosa Canina (Rose) Hips Oil, Sorbitan Olivate, Theobroma Cacao (Cocoa)Butter, Tocopheryl Acetate (Vitamin E), Xanthan Gum, Zemea (Corn) Propanediol

Questions?

Please visit our website, www.etaderm.com